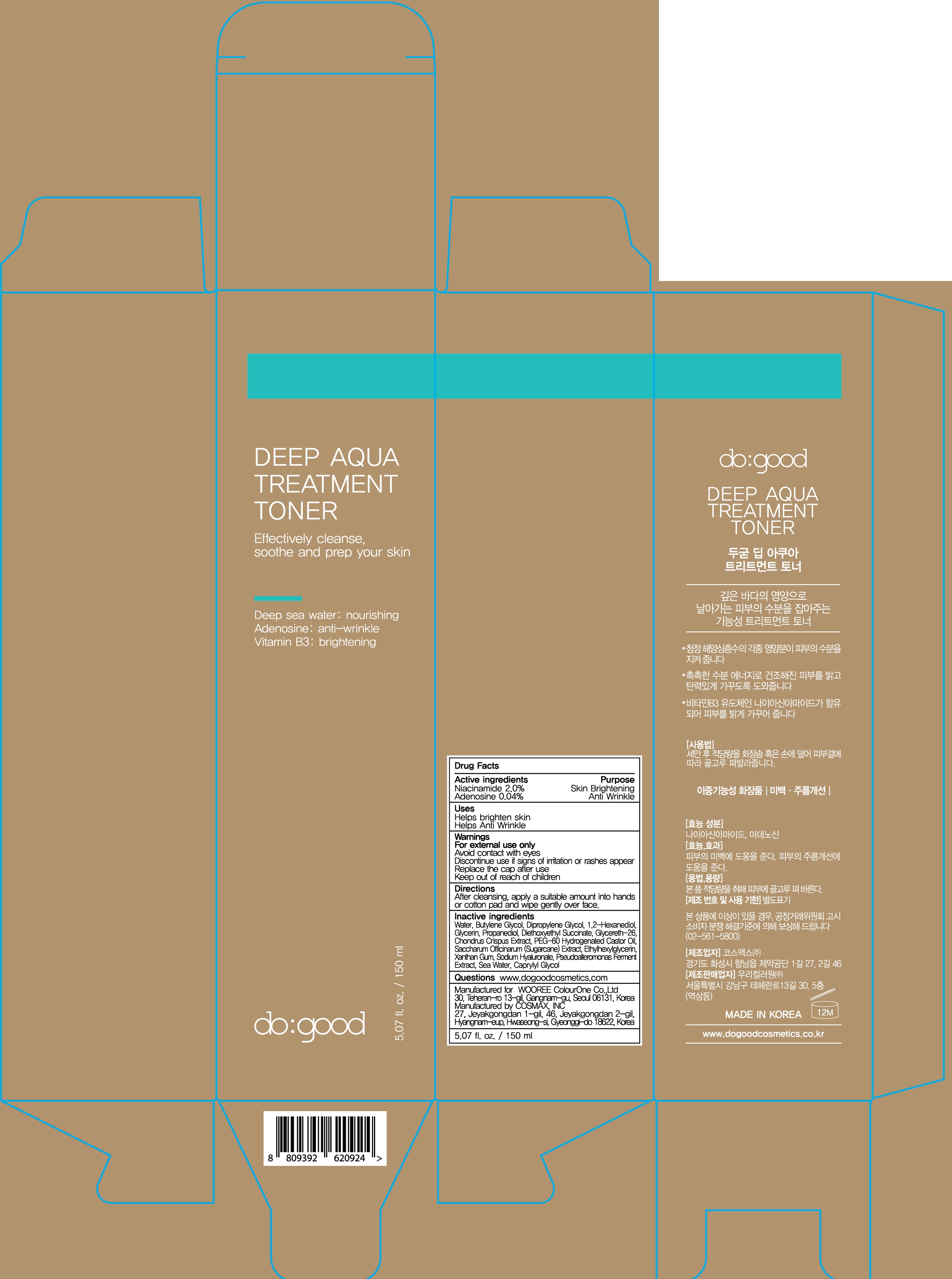 DRUG LABEL: do good Deep Aqua Treatment Toner
NDC: 72058-050 | Form: LIQUID
Manufacturer: WOOREE Colourone Co.,Ltd
Category: otc | Type: HUMAN OTC DRUG LABEL
Date: 20180222

ACTIVE INGREDIENTS: Niacinamide 3.00 g/150 mL; Adenosine 0.06 g/150 mL
INACTIVE INGREDIENTS: Water; Butylene Glycol

ACTIVE INGREDIENT

Active ingredients: Niacinamide 2.0%, Adenosine 0.04%

INACTIVE INGREDIENT

Inactive ingredients:

Water, Butylene Glycol, Dipropylene Glycol, 1,2-Hexanediol, Glycerin, Propanediol, Diethoxyethyl Succinate, Glycereth-26, Chondrus Crispus Extract, PEG-60 Hydrogenated Castor Oil, Saccharum Officinarum (Sugarcane) Extract, Ethylhexylglycerin, Xanthan Gum, Sodium Hyaluronate, Pseudoalteromonas Ferment Extract, Sea Water, Caprylyl Glycol

PURPOSE

Purpose: Skin Brightening, Anti wrinkle

WARNINGS

For external use only.

Avoid contact with eyes.

Discontinue use if signs of irritation or rashes appear.

Replace the cap after use.

Keep out of reach of children

KEEP OUT OF REACH OF CHILDREN

Uses

- Helps brighten skin

- Helps Anti Wrinkle

Directions

After cleansing, apply a suitable amount into hands or cotton pad and wipe gently over face.